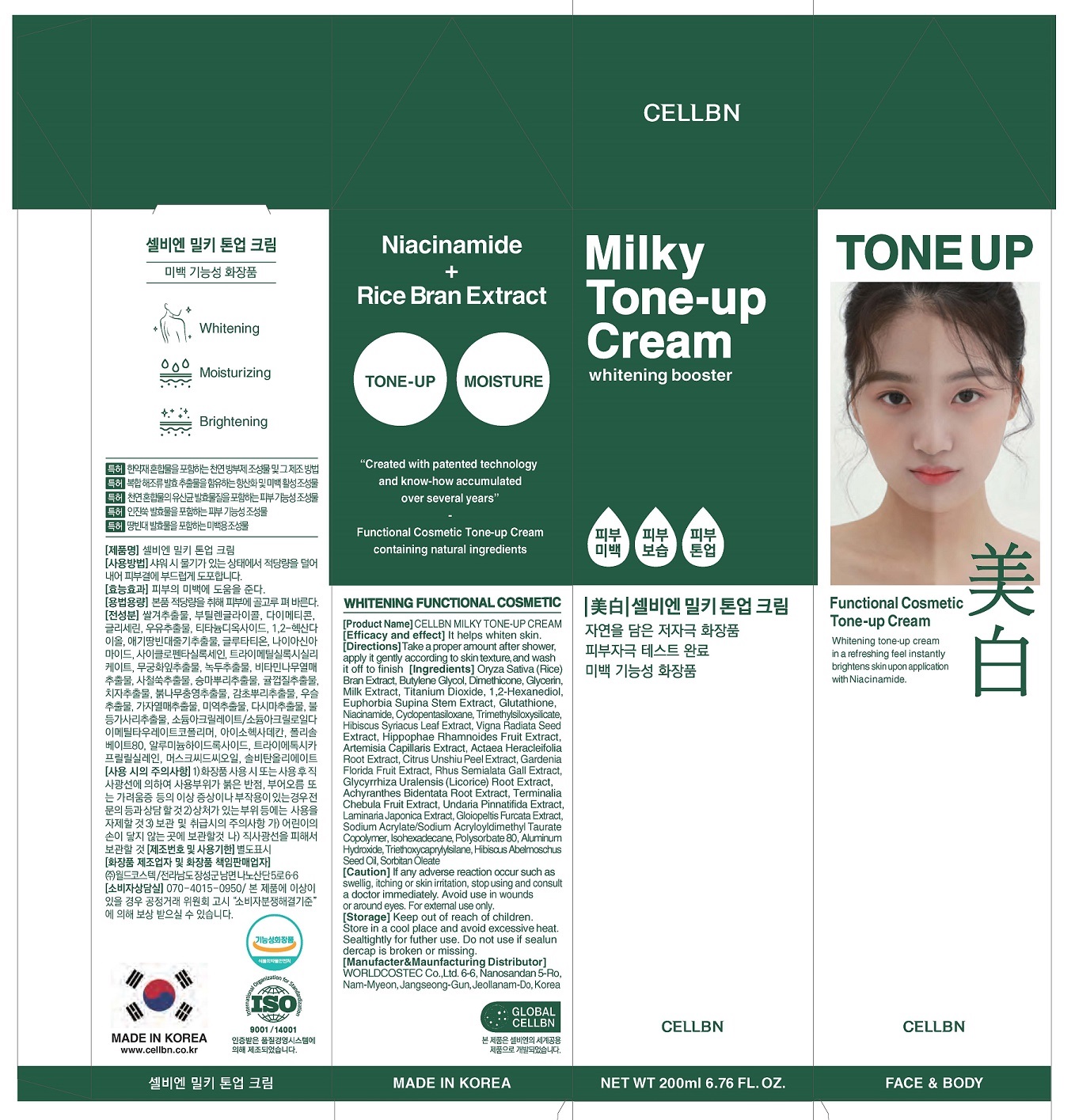 DRUG LABEL: CELLBN MILKY TONE-UPCREAM
NDC: 71450-0015 | Form: CREAM
Manufacturer: WORLDCOSTEC.CO.,LTD
Category: otc | Type: HUMAN OTC DRUG LABEL
Date: 20210810

ACTIVE INGREDIENTS: NIACINAMIDE 2 g/100 mL
INACTIVE INGREDIENTS: BUTYLENE GLYCOL; DIMETHICONE

ACTIVE INGREDIENT

niacinamide

INACTIVE INGREDIENT

Oryza Sativa (Rice) Bran Extract, Butylene Glycol, Dimethicone, Glycerin, Milk Extract, Titanium Dioxide, 1,2-Hexanediol, Euphorbia Supina Stem Extract, Glutathione, Cyclopentasiloxane, Trimethylsiloxysilicate, Hibiscus Syriacus Leaf Extract, VignaRadiata Seed Extract, HippophaeRhamnoides Fruit Extract, Artemisia Capillaris Extract, ActaeaHeracleifolia Root Extract, Citrus Unshiu Peel Extract, Gardenia Florida Fruit Extract, RhusSemialata Gall Extract, GlycyrrhizaUralensis (Licorice) Root Extract, AchyranthesBidentata Root Extract, Terminalia Chebula Fruit Extract, UndariaPinnatifida Extract, Laminaria Japonica Extract, GloiopeltisFurcata Extract, Sodium Acrylate/Sodium AcryloyldimethylTaurate Copolymer, Isohexadecane, Polysorbate 80, Aluminum Hydroxide, Triethoxycaprylylsilane, Hibiscus Abelmoschus Seed Oil, SorbitanOleate

PURPOSE

It Helps whiten skin

Keep out of reach of the children

INDICATIONS AND USAGE

Take a proper amount after shower apply it gently according to skin texture, and wash it off to finish

WARNINGS

1. Do not use in the following cases(Eczema and scalp wounds)
2.Side Effects
1)Due to the use of this druf if rash, irritation, itching and symptopms of hypersnesitivity occur dicontinue use and consult your phamacisr or doctor
3.General Precautions
1)If in contact with the eyes, wash out thoroughty with water If the symptoms are servere, seek medical advice immediately
2)This product is for exeternal use only. Do not use for internal use
4.Storage and handling precautions
1)If possible, avoid direct sunlight and store in cool and area of low humidity
2)In order to maintain the quality of the product and avoid misuse
3)Avoid placing the product near fire and store out in reach of children

DOSAGE AND ADMINISTRATION

for external use only